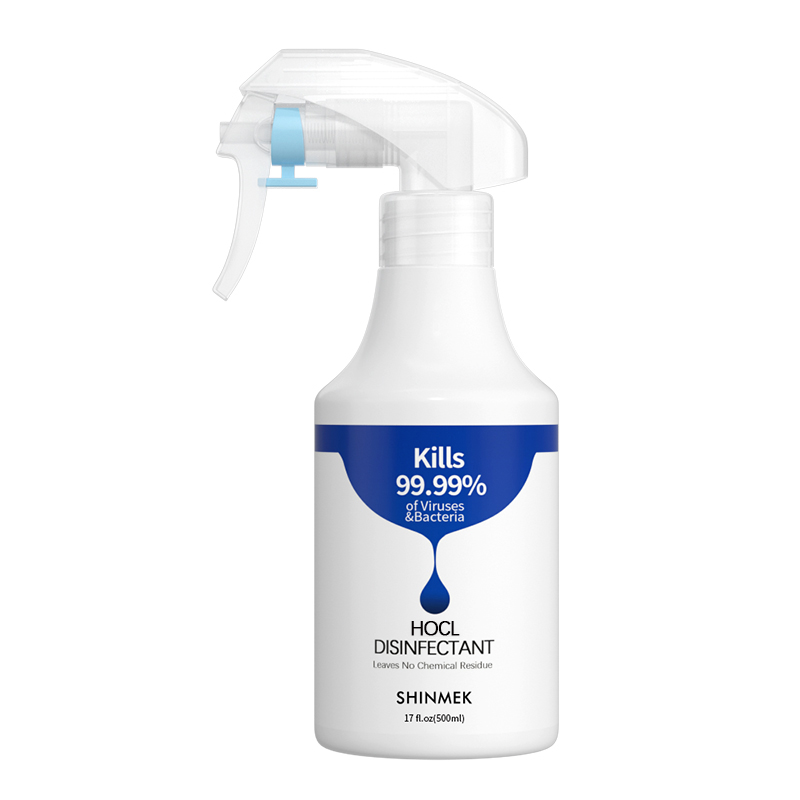 DRUG LABEL: Disinfectant
NDC: 82377-201 | Form: LIQUID
Manufacturer: Jinhua Shuxin Pharmaceutical Biotechnology Co., Ltd.
Category: otc | Type: HUMAN OTC DRUG LABEL
Date: 20230130

ACTIVE INGREDIENTS: HYPOCHLOROUS ACID 0.01 g/100 mL
INACTIVE INGREDIENTS: WATER

Disinfectant

Disinfectant

Active Ingredient(s)

HOCLl 0.01% g/mL. Purpose: Antiseptic

Purpose

Disinfectant

Use

Disinfectant to help reduce bacteria that potentially can cause disease.

Warnings

For external use only.

Do not use

- in children less than 2 months of age
- on open skin wounds

When using this product keep out of eyes, ears, and mouth. In case of contact with eyes, rinse eyes thoroughly with water.
Stop use and ask a doctor if irritation or rash occurs. These may be signs of a serious condition.
Keep out of reach of children. If swallowed, get medical help or contact a Poison Control Center right away.

Stop use and ask a doctor if irritation or rash occurs. These may be signs of a serious condition.

Keep out of reach of children. If swallowed, get medical help or contact a Poison Control Center right away.

Directions

- Spray on the skin 3-5 times each use. No rinsing reqiured.

Other information

- Store between 15-30C (59-86F)

Inactive ingredients

WATER